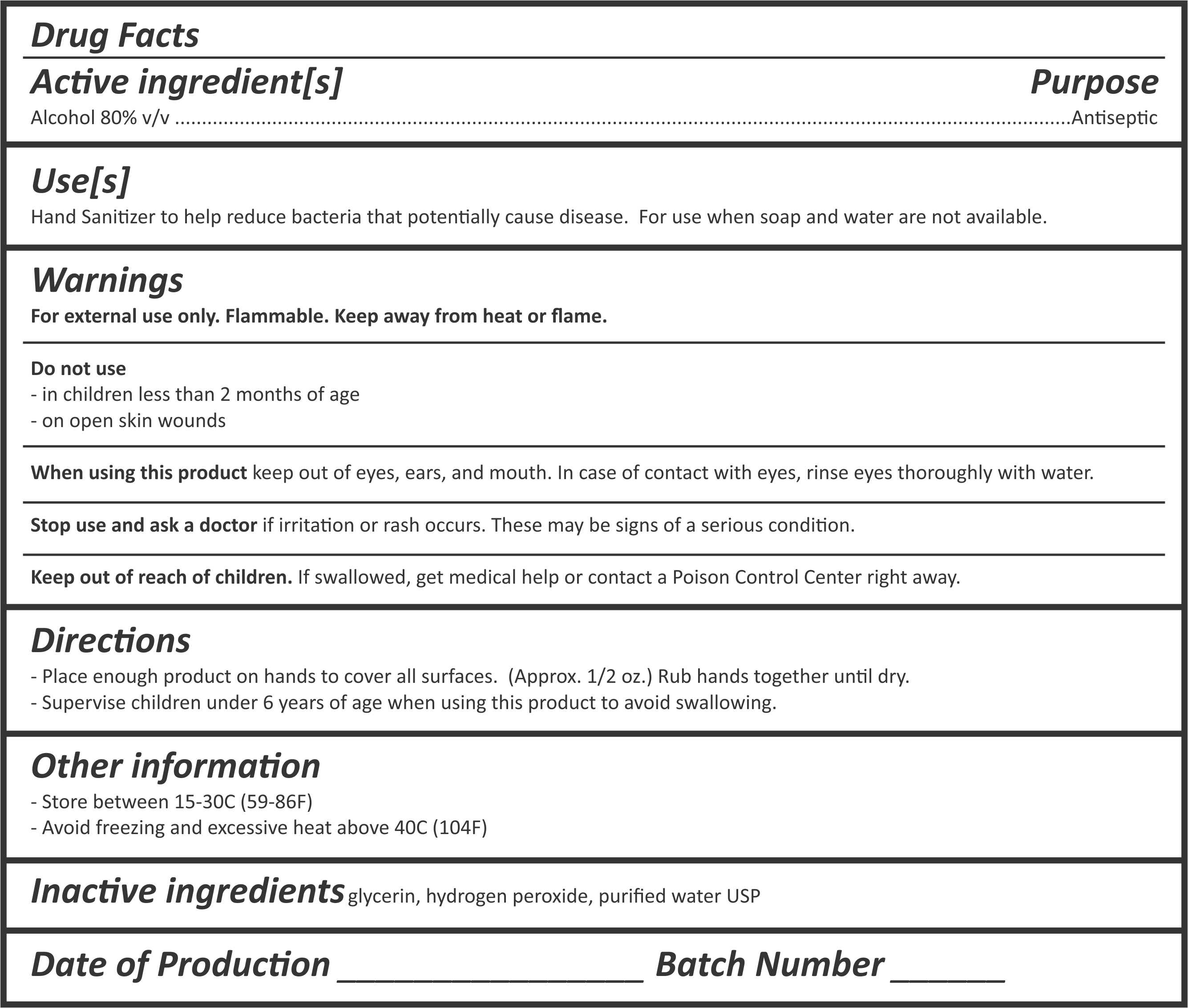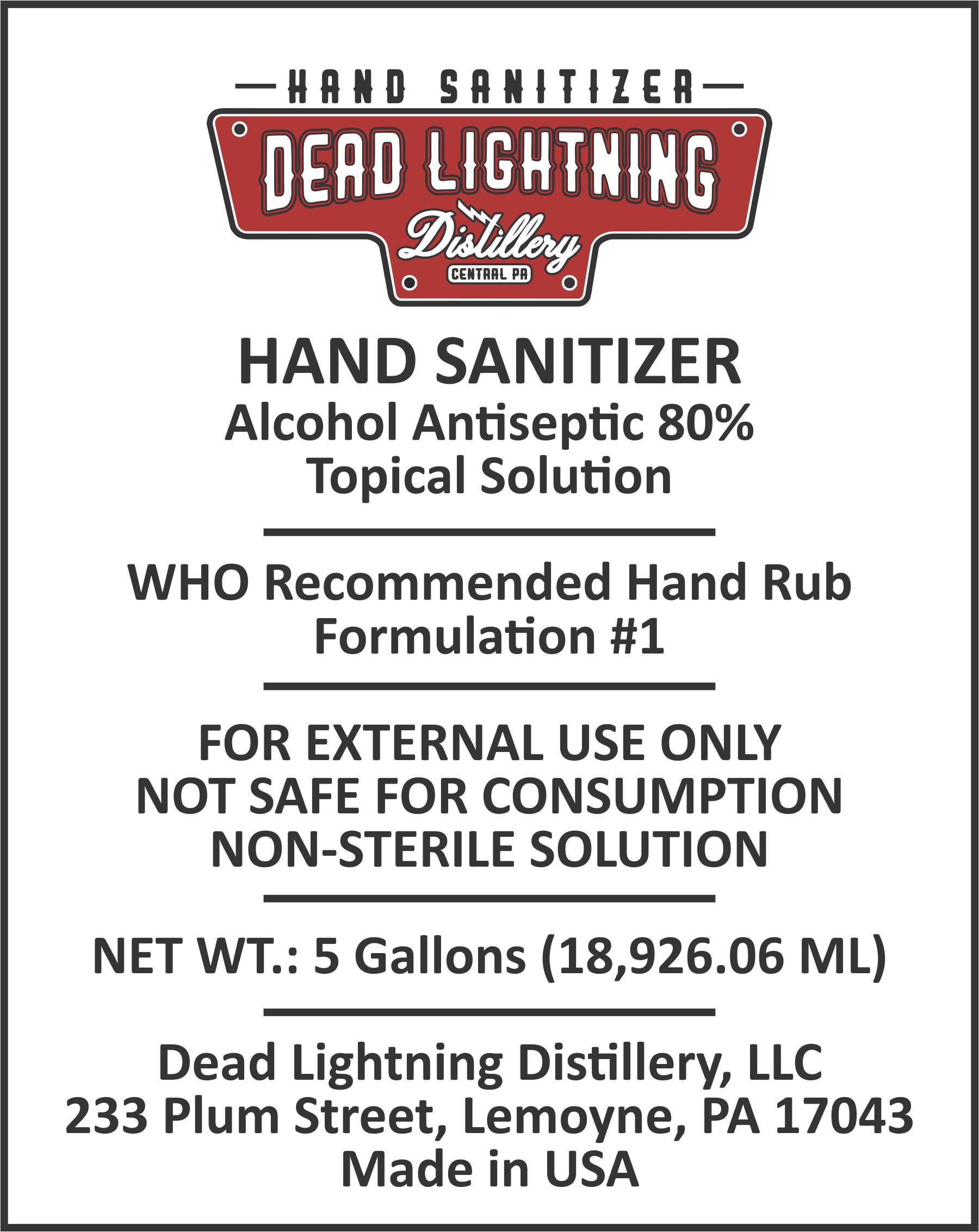 DRUG LABEL: Dead Lightning - Hand Sanitizer
NDC: 75451-001 | Form: LIQUID
Manufacturer: Dead Lightning Distillery, llc
Category: otc | Type: HUMAN OTC DRUG LABEL
Date: 20200421

ACTIVE INGREDIENTS: ALCOHOL 141.6 mL/177 mL
INACTIVE INGREDIENTS: HYDROGEN PEROXIDE 0.23 mL/177 mL; WATER 32.6 mL/177 mL; GLYCEROL FORMAL 2.57 mL/177 mL

Active Ingredients & Back Label

Active ingredient[s]
Alcohol 80% v/v .................Antiseptic

Purpose Section

Use[s]
Hand Sanitizer to help reduce bacteria that potentially cause disease. For use when soap and water are not available.

Indications and usage section

Hand Sanitizer to help reduce bacteria that potentially cause disease. For use when soap and water are not available.

Warnings section

Warnings
For external use only. Flammable. Keep away from heat or flame.

Do not use section

Do not use
- in children less than 2 months of age
- on open skin wounds

When using section

When using this product keep out of eyes, ears, and mouth. In case of contact with eyes, rinse eyes thoroughly with water.

Stop use section

Stop use and ask a doctor if irritation or rash occurs. These may be signs of a serious condition.

Keep out of reach of children section

Keep out of reach of children. If swallowed, get medical help or contact a Poison Control Center right away.

Directions section

Directions
- Place enough product on hands to cover all surfaces. Rub hands together until dry.
- Supervise children under 6 years of age when using this product to avoid swallowing.

Dosage and Administration

Place enough product on hands to cover all surfaces. (Approx. 1/2 oz.) Rub hands together until dry.

Other safety information

Other information
- Store between 15-30C (59-86F)
- Avoid freezing and excessive heat above 40C (104F)

Inactive ingredients section

Inactive ingredients glycerin, hydrogen peroxide, purified water USP

Date of Production & Batch Number

Date of Production

Batch Number

Principal display panel & front label

Dead Lightning Logo

HAND SANITIZER
Alcohol Antiseptic 80%
Topical Solution
WHO Recommended Hand Rub
Formulation #1
FOR EXTERNAL USE ONLY
NOT SAFE FOR CONSUMPTION
NON-STERILE SOLUTION
NET WT.: 5 Gallons (18,926.06 ML)
Dead Lightning Distillery, LLC
233 Plum Street, Lemoyne, PA 17043
Made in USA